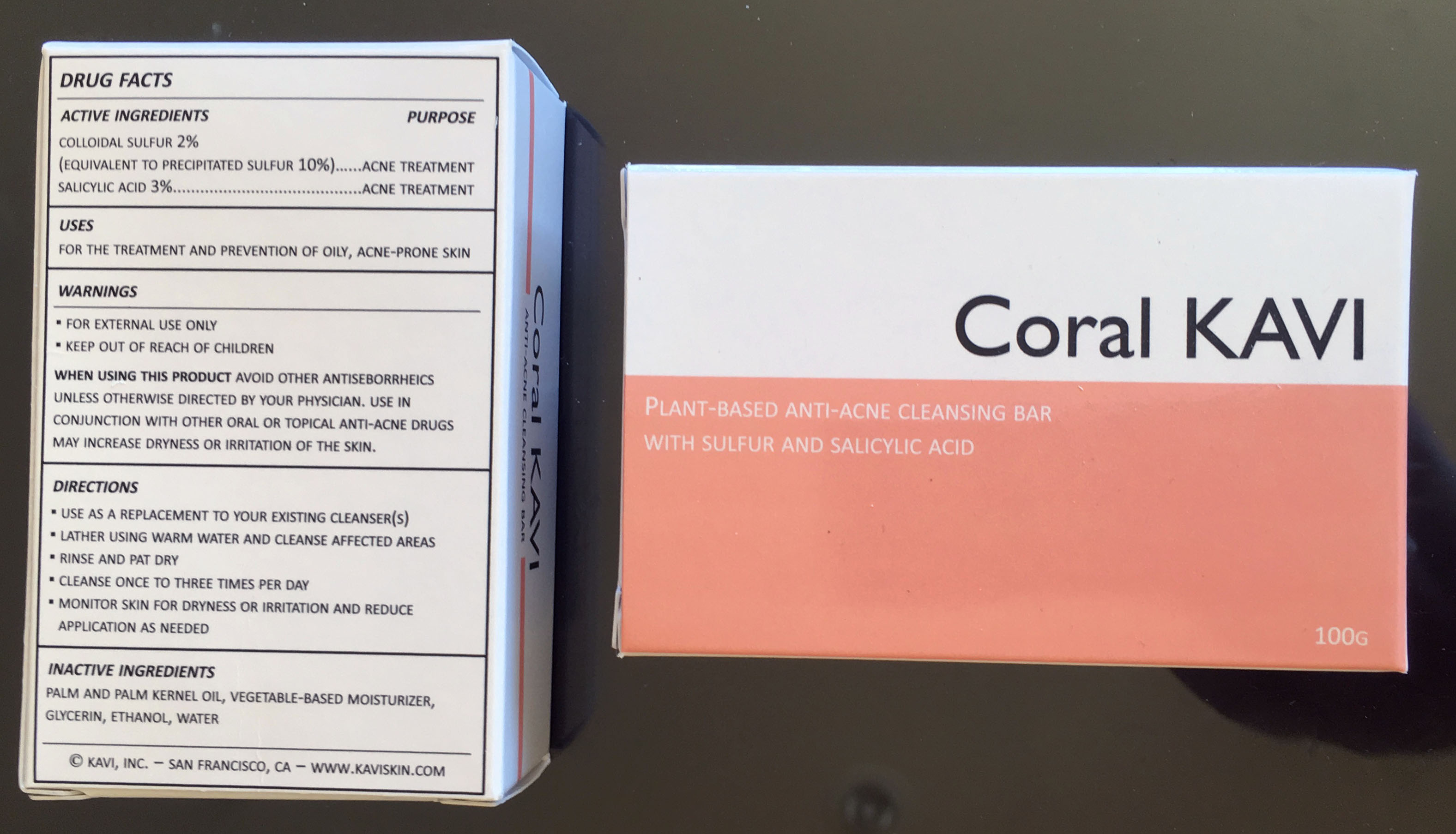 DRUG LABEL: Coral KAVI
NDC: 42771-0001 | Form: SOAP
Manufacturer: KAVI Skin Solutions, Inc.
Category: otc | Type: HUMAN OTC DRUG LABEL
Date: 20201020

ACTIVE INGREDIENTS: SULFUR 2 g/100 g; SALICYLIC ACID 3 g/100 g
INACTIVE INGREDIENTS: HYDROGENATED PALM OIL 90 g/100 g; SODIUM COCOYL ISETHIONATE 1 g/100 g; ALCOHOL 1 g/100 g; GLYCERIN 1 g/100 g; 1,2-BUTANEDIOL 0.5 g/100 g; TITANIUM DIOXIDE 0.25 g/100 g

Coral KAVI

active ingredients, purpose

colloidal sulfur 2%
(equivalent to precipitated sulfur 10%)…...acne treatment
salicylic acid 3%.........................................acne treatment

Indications & Usage

uses
for the treatment and prevention of oily, acne-prone skin

directions

▪ use as a replacement to your existing cleanser(s)
▪ lather using warm water and cleanse affected areas
▪ rinse and pat dry
▪ cleanse once to three times per day
▪ monitor skin for dryness or irritation and reduce application as needed

Dosage and Administration

▪ use as a replacement to your existing cleanser(s)
▪ lather using warm water and cleanse affected areas
▪ rinse and pat dry
▪ cleanse once to three times per day
▪ monitor skin for dryness or irritation and reduce application as needed

Warnings

▪ for external use only
▪ keep out of reach of children

when using this product avoid other antiseborrheics unless otherwise directed by your physician. use in conjunction with other oral or topical anti-acne drugs may increase dryness or irritation of the skin.

inactive ingredients

palm and palm kernel oil, vegetable-based moisturizer, glycerin, ethanol, water

Purpose

for the treatment and prevention of oily, acne-prone skin

Keep out of reach of children

▪ for external use only
▪ keep out of reach of children

Active Ingredients, Uses, Warnings, Directions, Inactive Ingredients

drug facts

active ingredients/purpose

colloidal sulfur 2%
(equivalent to precipitated sulfur 10%)…...acne treatment
salicylic acid 3%.........................................acne treatment

uses
for the treatment and prevention of oily, acne-prone skin

warnings

▪ for external use only
▪ keep out of reach of children

when using this product avoid other antiseborrheics unless otherwise directed by your physician. use in conjunction with other oral or topical anti-acne drugs may increase dryness or irritation of the skin.

directions

▪ use as a replacement to your existing cleanser(s)
▪ lather using warm water and cleanse affected areas
▪ rinse and pat dry
▪ cleanse once to three times per day
▪ monitor skin for dryness or irritation and reduce application as needed

inactive ingredients

palm and palm kernel oil, vegetable-based moisturizer, glycerin, ethanol, water